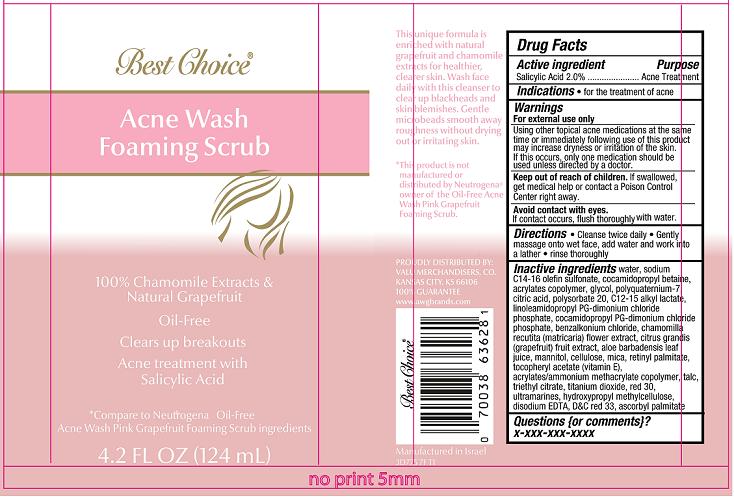 DRUG LABEL: Best Choice Oil-Free Acne Wash Foaming Scrub
NDC: 63941-775 | Form: LOTION
Manufacturer: Valu Merchandisers Company
Category: otc | Type: HUMAN OTC DRUG LABEL
Date: 20130206

ACTIVE INGREDIENTS: SALICYLIC ACID 20 mg/1 mL
INACTIVE INGREDIENTS: WATER; SODIUM C14-16 OLEFIN SULFONATE; COCAMIDOPROPYL BETAINE; PROPYLENE GLYCOL; C12-15 ALKYL LACTATE; COCAMIDOPROPYL PG-DIMONIUM CHLORIDE PHOSPHATE; BENZALKONIUM CHLORIDE; CHAMOMILE; ALOE VERA LEAF; EDETATE DISODIUM; CARBOMER COPOLYMER TYPE A (ALLYL PENTAERYTHRITOL CROSSLINKED); GLYCERIN; SODIUM HYDROXIDE; POLYQUATERNIUM-7 (70/30 ACRYLAMIDE/DADMAC; 1600000 MW); CITRIC ACID MONOHYDRATE; POLYSORBATE 20; LINOLEAMIDOPROPYL PG-DIMONIUM CHLORIDE PHOSPHATE; PUMMELO; MANNITOL; CELLULOSE, MICROCRYSTALLINE; MICA; VITAMIN A PALMITATE; .ALPHA.-TOCOPHEROL ACETATE; TALC; TRIETHYL CITRATE; TITANIUM DIOXIDE; D&C RED NO. 30; ULTRAMARINE BLUE; HYPROMELLOSE 2208 (100 MPA.S); D&C RED NO. 33; ASCORBYL PALMITATE

Best Choice® Oil-Free Acne Wash Foaming Scrub

Active ingredient

Salicylic Acid 2.0%

Purpose

Acne Treatment

Indications

- for the treatment of acne

Warnings

For external use only.

Using other topical acne medications at the same time or immediately following use of this product may increase dryness or irritation of the skin. If this occurs, only one medication should be used unless directed by a doctor.

Keep Out of Reach of Children.

If swallowed, get medical help or contact a Poison Control Center right away. Avoid contact with eyes. If contact occurs, flush thoroughly with water.

Directions

- Clean twice daily
- Gently massage onto wet face, add water and work into a lather
- Rinse thoroughly

Inactive ingredients

water, sodium C14-16 olefin sulfonate, cocamidopropyl betaine, acrylates copolymer, glycol, polyquaternium-7, citric acid, polysorbate 20, C12-15 alkyl lactate, linoleamidopropyl PG-dimonium chloride phosphate, cocamidopropyl PG-dimonium chloride phosphate, benzalkonium chloride, chamomilla recutita (matricaria) flower extract, citrus grandis (grapefruit) fruit extract, aloe barbadensis leaf juice, mannitol, cellulose, mica, retinyl palmitate, tocopheryl acetate (vitamin E), acrylates/ammonium methacrylate copolymer, talc, triethyl citrate, titanium dioxide, red 30, ultramarines, hydroxypropyl methylcellulose, disodium EDTA, D&C red 33, ascorbyl palmitate

Package/Label Principal Display Panel

Best Choice® Oil-Free Acne Wash Foaming Scrub

100% Chamomile Extracts & Natural Grapefruit

Oil-Free

Clears up breakouts

Acne Treatment with Salicylic Acid

*Compare to Neutrogena® Oil-Free
Acne Wash Pink Grapefruit Foaming Scrub Ingredients

4.2 Fl Oz (124 mL)

PROUDLY DISTRIBUTED BY:
VALU MERCHANDISERS, CO.
KANSAS CITY, KS 66106
100% GUARANTEE

www.awgbrands.com

Manufactured in Israel
3D775 7FT1

Carton Label